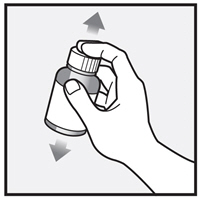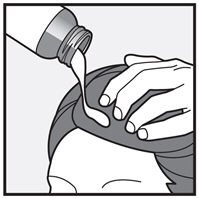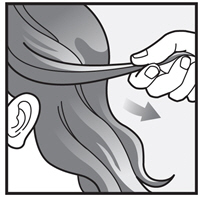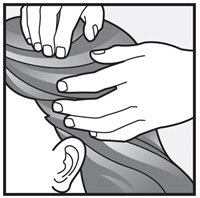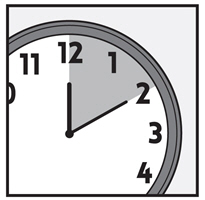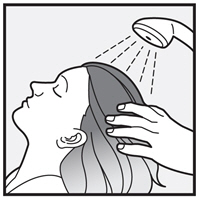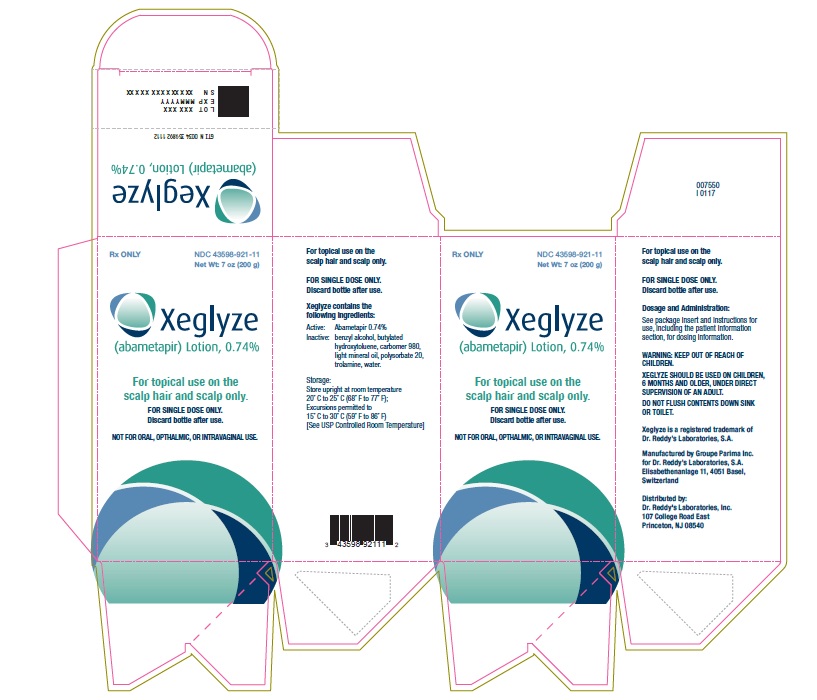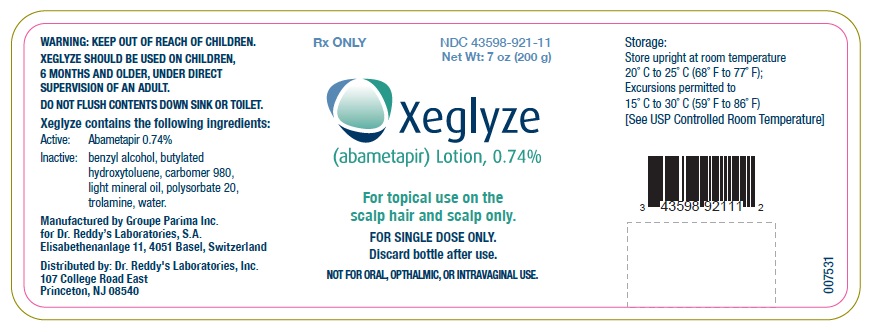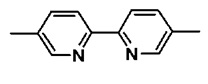 DRUG LABEL: Xeglyze
NDC: 43598-921 | Form: LOTION
Manufacturer: Dr. Reddy's Laboratories Inc.
Category: prescription | Type: HUMAN PRESCRIPTION DRUG LABEL
Date: 20240730

ACTIVE INGREDIENTS: Abametapir  0.74 g/100 g
INACTIVE INGREDIENTS: Water; Polysorbate 20; CARBOMER HOMOPOLYMER TYPE C; Trolamine; Butylated Hydroxytoluene; Benzyl Alcohol; Light Mineral Oil

HIGHLIGHTS OF PRESCRIBING INFORMATION

These highlights do not include all the information needed to use XEGLYZETM safely and effectively. See full prescribing information for XEGLYZE.
XEGLYZE (abametapir) lotion, for topical use
Initial U.S. Approval: 2020

1 INDICATIONS AND USAGE

XEGLYZE is a pediculicide indicated for the topical treatment of head lice infestation in patients 6 months of age and older. XEGLYZE should be used in the context of an overall lice management program:

- Wash (with hot water) or dry-clean all recently worn clothing, hats, used bedding and towels
- Wash personal care items such as combs, brushes and hair clips in hot water
- Use a fine-tooth comb or special nit comb to remove dead lice and nits (1)

2 DOSAGE AND ADMINISTRATION

- For topical use only. Not for oral, ophthalmic, or intravaginal use. (2)
- Shake well before use. (2)
- Apply XEGLYZE to dry hair in an amount sufficient (up to the full content of one bottle) to thoroughly coat the hair and scalp. Avoid contact with eyes. (2)
- Massage XEGLYZE into the scalp and throughout the hair; leave on the hair and scalp for 10 minutes and then rinse off with warm water. (2)
- Massage XEGLYZE into the scalp and throughout the hair; leave on the hair and scalp for 10 minutes and then rinse off with warm water. (2)

3 DOSAGE FORMS AND STRENGTHS

Lotion: 0.74% [weight by weight]. (3)

4 CONTRAINDICATIONS

None. (4)

5 WARNINGS AND PRECAUTIONS

- Risk of Neonatal Benzyl Alcohol Toxicity: Systemic exposure to benzyl alcohol has been associated with serious adverse reactions and death in neonates and low birth-weight infants. Safety and effectiveness in pediatric patients below the age of 6 months have not been established. Use is not recommended in pediatric patients under 6 months of age because of the potential for increased systemic absorption. (5.1)
- Risk of Benzyl Alcohol Toxicity from Accidental Ingestion: Administer only under direct supervision of an adult. (5.2)

6 ADVERSE REACTIONS

Most common adverse reactions (incidence of ≥ 1%) were erythema, rash, skin burning sensation, contact dermatitis, vomiting, eye irritation, pruritus, and hair color changes. (6.1)

To report SUSPECTED ADVERSE REACTIONS, contact Dr. Reddy’s Laboratories. Inc., at 1-888-966-8766 or FDA at 1-800-FDA-1088 or www.fda.gov/medwatch.

7 DRUG INTERACTIONS

For 2 weeks after XEGLYZE application, avoid taking drugs that are substrates of CYP3A4, CYP2B6 or CYP1A2. Otherwise, avoid use of XEGLYZE. (7)

FULL PRESCRIBING INFORMATION

1 INDICATIONS AND USAGE

XEGLYZE is indicated for the topical treatment of head lice infestation in patients 6 months of age and older.

XEGLYZE should be used in the context of an overall lice management program:

- Wash (with hot water) or dry-clean all recently worn clothing, hats, used bedding and towels
- Wash personal care items such as combs, brushes, and hair clips in hot water

Use a fine-tooth comb or special nit comb to remove dead lice and nits

2 DOSAGE AND ADMINISTRATION

For topical use only. XEGLYZE is not for oral, ophthalmic, or intravaginal use. Treatment with XEGLYZE involves a single application.

Shake well before use. Apply XEGLYZE to dry hair in an amount (up to the full content of one bottle) sufficient to thoroughly coat the hair and scalp. Massage XEGLYZE into the scalp and throughout the hair. Avoid contact with eyes. Leave on the hair and scalp for 10 minutes and then rinse off with warm water. Wash hands after application. Hair may be shampooed any time after the treatment.

Discard any unused product. Do not flush contents down sink or toilet.

3 DOSAGE FORMS AND STRENGTHS

Lotion, 0.74% [weight by weight], a viscous white to off-white oil in water emulsion, containing abametapir.

4 CONTRAINDICATIONS

None.

5 WARNINGS AND PRECAUTIONS

5.1 Risk of Neonatal Benzyl Alcohol Toxicity

XEGLYZE contains benzyl alcohol. Systemic exposure to benzyl alcohol has been associated with serious and fatal adverse reactions including “gasping syndrome” in neonates and low birth weight infants. The “gasping syndrome” is characterized by central nervous system depression, metabolic acidosis, and gasping respirations. The minimum amount of benzyl alcohol at which toxicity may occur is not known. Premature and low-birth weight infants may be more likely to develop toxicity [see Use in Specific Populations (8.4)].

The safety and effectiveness of XEGLYZE have not been established in pediatric patients below the age of 6 months. Use is not recommended in pediatric patients under 6 months of age because of the potential for increased systemic absorption.

5.2 Risk of Benzyl Alcohol Toxicity from Accidental Ingestion

In order to prevent accidental ingestion in pediatric patients, XEGLYZE should only be administered under direct supervision of an adult.

Ingestion of benzyl alcohol in large quantities may result in gastrointestinal (nausea, vomiting, diarrhea) and central nervous system (headache, ataxia, convulsions, coma) adverse reactions. Serious adverse reactions may include respiratory depression and death. If accidentally swallowed, advise the patient or the caregiver to call their Poison Control Center at 1-800-222-1222.

6 ADVERSE REACTIONS

6.1 Clinical Trials Experience

Because clinical trials are conducted under widely varying conditions, adverse reaction rates observed in the clinical trials of a drug cannot be directly compared to the rates in the clinical trials of another drug, and may not reflect the rates observed in practice.

The data described below reflect exposure to a single 10-minute treatment of XEGLYZE in 349 subjects (6 months of age and older) with head lice infestation in randomized, double-blind, vehicle-controlled trials (Trials 1 and 2). Of these subjects, 21 were 6 months to 4 years of age, 166 subjects were 4 to 12 years of age, 57 subjects were 12 to 18 years of age, and 105 subjects were 18 years of age or older.

Table 1 provides adverse reactions that occurred in at least 1% of subjects in the XEGLYZE group and at a greater frequency than in the vehicle group.

Table 1: Adverse Reactions Occurring in ≥ 1% of the XEGLYZE Group and at a Greater Frequency than in the Vehicle Group (Trials 1 and 2)

Adverse Reactions | XEGLYZE N=349 Subjects (%) | Vehicle N=350 Subjects (%)
Erythema | 14 (4.0) | 6 (2)
Rash | 11 (3.2) | 8 (2.3)
Skin burning sensation | 9 (2.6) | 0 (0.0)
Contact dermatitis | 6 (1.7) | 4 (1.1)
Vomiting | 6 (1.7) | 2 (0.6)
Eye irritation | 4 (1.2) | 2 (0.6)
Hair color changes | 3 (1) | 0 (0.0)

During the trials, subjects were monitored for new onset of scalp erythema/edema, scalp pruritus, and eye irritation. The number and percentage of subjects who developed these local adverse reactions after treatment are presented in Table 2.

Table 2: Monitored Local Adverse Reactions with New Onset on Day 1 Post-Treatment (Trials 1 and 2)

Adverse Reactions | XEGLYZE Subjects (%)* | Vehicle Subjects (%)*
Scalp Erythema/Edema | 11 (3.2) | 5 (1.4)
Scalp Pruritus | 2 (1.4) | 1 (0.7)
Eye Irritation | 6 (1.7) | 5 (1.4)

* For the calculation of the percentages, the denominators are the number of subjects who did not have the monitored local adverse reaction at baseline.

7 DRUG INTERACTIONS

In vitro studies suggest there is a potential for inhibition of cytochrome P450 (CYP) 3A4, 2B6 and 1A2 enzymes following a single application of XEGLYZE. Use of XEGLYZE with drugs that are substrates of these enzymes may lead to increased systemic concentrations of the interacting drugs. Avoid administration of drugs that are substrates of CYP3A4, CYP2B6, or CYP1A2 within 2 weeks after application of XEGLYZE. If this is not feasible, avoid use of XEGLYZE [see Clinical Pharmacology (12.3)].

8 USE IN SPECIFIC POPULATIONS

8.1 Pregnancy

Risk Summary

There are no available data on XEGLYZE use in pregnant women to evaluate for a drug-associated risk of major birth defects, miscarriage, or adverse maternal or fetal outcomes. In embryofetal development studies conducted with oral administration of abametapir during organogenesis, no evidence of fetal harm or malformations, independent of maternal toxicity were observed in pregnant rats and rabbits at doses that produced exposures up to 50 times and equivalent to the maximum recommended human dose (MRHD) in rats and rabbits, respectively. The highest dose evaluated in rabbits was limited due to maternal toxicity associated with the vehicle used in the study (see Data).

The background risk of major birth defects and miscarriage for the indicated population is unknown. In the U.S. general population, the estimated background risk of major birth defects and miscarriage in clinically recognized pregnancies is 2 to 4% and 15 to 20%, respectively.

Data

Animal Data

Systemic embryofetal development studies were performed in rats and rabbits. Oral doses of 10, 25 and 75 mg/kg/day abametapir were administered during the period of organogenesis (gestational days 6 – 17) to pregnant rats. In the presence of maternal toxicity, embryofetal toxicity (lower fetal body weights and delayed ossification) was noted at 75 mg/kg/day. No treatment related effects on malformations were noted at 75 mg/kg/day (50 times the MRHD based on Cmax comparisons).

Oral doses of 4, 16 and 40 mg/kg/day abametapir were administered during the period of organogenesis (gestational days 6 – 19) to pregnant rabbits. No treatment related effects on embryofetal toxicity or malformations were noted at 40 mg/kg/day (~1 time the MRHD based on Cmax comparisons). Maternal toxicity related to the vehicle limited the maximum dose in pregnant rabbits.

In a perinatal and postnatal development study in rats, oral doses of 10, 25 and 75 mg/kg/day were administered from the beginning of organogenesis (gestational day 6) through the end of lactation (lactation day 20). In the presence of maternal toxicity, embryofetal lethality, and decreased fetal body weight gain were noted at 75 mg/kg/day. No treatment related effects on postnatal development were noted at 75 mg/kg/day (47 times the MRHD based on Cmax comparisons).

8.2 Labor and Delivery

Risk Summary

No data are available regarding the presence of abametapir in human milk or the effects of abametapir on the breastfed infant or on milk production. The developmental and health benefits of breastfeeding should be considered along with the mother’s clinical need for XEGLYZE and any potential adverse effects on the breastfed child from XEGLYZE or from the underlying maternal condition.

8.4 Pediatric Use

The safety and effectiveness of XEGLYZE have been established in pediatric patients 6 months of age and older [see Clinical Pharmacology (12) and Clinical Studies (14)].

The safety and effectiveness of XEGLYZE have not been established in pediatric patients below the age of 6 months. XEGLYZE is not recommended in pediatric patients under 6 months of age because of the potential for increased systemic absorption due to a high ratio of skin surface to body mass and the potential for an immature skin barrier.

XEGLYZE contains benzyl alcohol. Benzyl alcohol has been associated with serious adverse reactions and death in neonates and low birth-weight infants. The “gasping syndrome” (characterized by central nervous system depression, metabolic acidosis, gasping respirations, and high levels of benzyl alcohol and its metabolites found in the blood and urine) has been associated with intravenously administered benzyl alcohol dosages >99 mg/kg/day in neonates and low birthweight infants. Additional symptoms may include gradual neurological deterioration, seizures, intracranial hemorrhage, hematologic abnormalities, skin breakdown, hepatic and renal failure, hypotension, bradycardia, and cardiovascular collapse.

The minimum amount of benzyl alcohol at which toxicity may occur is not known. Premature and low-birthweight infants, as well as patients receiving high dosages, may be more likely to develop toxicity [see Warnings and Precautions (5.1)].

Because of the risk of accidental ingestion, XEGLYZE should be administered to pediatric patients only under direct adult supervision [see Warnings and Precautions (5.2)].

8.5 Geriatric Use

Clinical studies of XEGLYZE did not include sufficient numbers of subjects aged 65 years and over to determine whether they respond differently from younger subjects. Other reported clinical experience has not identified differences in responses between elderly and younger subjects.

10 OVERDOSAGE

If accidentally swallowed, advise patients to seek medical advice immediately and to call their local Poison Control Center at 1-800-222-1222.

11 DESCRIPTION

The active pharmacological ingredient in XEGLYZE (abametapir) Lotion is the pediculicide, abametapir, which is a dipyridyl compound. The chemical name of abametapir is 5,5'-dimethyl-2,2'-bipyridinyl.

The structural formula is:

The empirical formula is C12H12N2 and the molecular weight is 184.24.

XEGLYZE is a white to off-white oil in water emulsion, containing 0.74% [weight by weight] of abametapir, intended for topical administration. XEGLYZE contains the following inactive ingredients: benzyl alcohol 2.0% , butylated hydroxytoluene, Carbomer Homopolymer Type C, light mineral oil, polysorbate 20, trolamine and water.

12 CLINICAL PHARMACOLOGY

12.1 Mechanism of Action

Abametapir (5,5’-dimethyl 2,2’-bipyridinyl) is a metalloproteinase inhibitor. Metalloproteinases have a role in physiological processes critical to egg development and survival of lice.

12.3 Pharmacokinetics

Absorption

The pharmacokinetics of XEGLYZE were evaluated in 3 trials, Trials A, B, and C. Each trial enrolled lice infested subjects who received a single 10-minute application of XEGLYZE. Pharmacokinetic samplings were carried out to 72 hours post-dose in adults and 8 hours post-dose in pediatric subjects in all trials.

Trial A evaluated pharmacokinetics in 6 adult and 12 pediatric subjects 3 to 12 years of age. The mean (%CV) abametapir plasma maximum concentration (Cmax) and area under the concentration time curve from 0 to 8 hours post-dose (AUC0-8h) in the adult group were 41 (66%) ng/mL and 121 (50%) ng*h/mL, respectively. The mean (%CV) Cmax and AUC0-8h in the pediatric group were 73 (57%) ng/mL and 264 (62%) ng*h/mL, respectively. The mean (%CV) terminal half-life in adults was 21 (11%) hours.

Trials B and C evaluated pharmacokinetics in 50 pediatric subjects 6 months to 17 years old. The pharmacokinetic results for plasma abametapir are shown in Table 3. Even though the values varied between the 2 trials, abametapir exposure increased as the age of the subject decreased. Abametapir absorption was rapid with a median Tmax of 0.57 to 1.54 hours.

Table 3 Abametapir Pharmacokinetic Parameters in Subjects with Head Lice Infestation

Study | Age Group | n | Cmax (ng/mL) Mean (%CV) | AUC0-8h (ng*h/mL) Mean (%CV)
B | 6 months to <1 year | 1 | 418 | 1057
C | 6 months to <1 year | 5 | 228 (50%) | 688 (43%)
B | 1 year to <2 years | 3 | 209 (62%) | 446 (65%)
C | 1 year to <2 years | 8 | 147 (49%) | 406 (37%)
B | 2 years to <3 years | 6 | 206 (66%) | 633 (57%)
C | 2 years to <3 years | 8 | 160 (48%) | 602 (51%)
B | 3 years to 17 years | 12 | 121 (60%) | 330 (49%)
C | 3 years to 17 years | 7 | 52 (45%) | 194 (39%)

Serum concentration of benzyl alcohol, an excipient in the formulation of XEGLYZE, was assessed in Trials B and C. Benzyl alcohol in serum was measurable (limit of quantitation = 0.5 µg/mL) in 7 subjects out of 39 evaluable subjects. The Cmax of benzyl alcohol in these 7 subjects ranged from 0.52 to 3.57 µg/mL [see Warnings and Precautions (5) and Use in Specific Populations (8.4)].

Distribution

Abametapir and its primary human metabolite, abametapir carboxyl, are highly bound to proteins in plasma. Abametapir is 91.3 – 92.3% bound to plasma proteins, and abametapir carboxyl is 96.0% – 97.5% bound to plasma proteins.

Elimination

Metabolism

Abametapir is extensively metabolized, primarily by the cytochrome P450 enzyme CYP1A2 to a mono-hydroxylated metabolite (abametapir hydroxyl) and further to a mono-carboxylated metabolite (abametapir carboxyl). Abametapir carboxyl is cleared slowly from the systemic circulation resulting in plasma concentration higher than that of abametapir. Based on data in adults in Trial A above, where sampling was carried out to 72 hours, the ratios of Cmax and AUC0-72h between abametapir carboxyl and abametapir were about 30 and 250, respectively. The elimination half-life of abametapir carboxyl has not been well characterized but is estimated to be approximately (mean ± SD) 71 ± 40 hours or longer in adults.

Excretion

Excretion of abametapir and its human metabolites was not examined in patients.

Drug Interaction Studies

In vitro studies suggest that there is a potential for inhibition of cytochrome P450 3A4, 2B6, and 1A2 enzymes following application of XEGLYZE due to high and prolonged systemic exposure of the metabolite abametapir carboxyl [see Drug Interactions (7)].

13 NONCLINICAL TOXICOLOGY

13.1 Carcinogenesis, Mutagenesis, Impairment Of Fertility

Long-term studies in animals have not been conducted to evaluate the carcinogenic potential of XEGLYZE or abametapir.

Abametapir was not mutagenic or clastogenic based on the results of two in vitro genotoxicity tests (Ames test and human lymphocyte chromosomal aberration assay) and one in vivo genotoxicity test (rat micronucleus assay).

No effects on fertility have been observed in rats following repeated oral doses of up to 75 mg/kg/dayabametapir (50 times the MRHD based on Cmax comparisons).

14 CLINICAL STUDIES

Two identical multi-center, randomized, double-blind, vehicle-controlled trials (Trials 1 and 2) were conducted in 704 subjects 6 months of age and older with head lice infestation. All subjects received a single application of either XEGLYZE or vehicle control. For the evaluation of efficacy, the youngest subject from each household was considered to be the index subject of the household (N=216). Other enrolled infested household members received the same treatment as the youngest subject and were evaluated for all efficacy and safety parameters. Index subjects ranged from 6 months to 49 years of age (mean 7 years), and approximately 85% of the index subjects were female, and 95% of the index subjects were Caucasian.

Efficacy was assessed as the proportion of index subjects who were treated with a single 10-minute application and were free of live lice at all follow-up visits on Days 1, 7, and 14. Subjects with live lice at any time up to the final evaluation were considered treatment failures. Table 4 presents the proportion of subjects who were free of live lice at all visits Day 1 through Day 14 in Trials 1 and 2.

Table 4: Proportion of Index Subjects Free of Live Lice at All Visits Days 1 Through 14 After Treatment

 | Trial 1 |  | Trial 2
 | XEGLYZE (N=53) | Vehicle (N=55) | XEGLYZE (N=55) | Vehicle (N=53)
Treatment Success | 43 (81.1%) | 28 (50.9%) | 45 (81.8%) | 25 (47.2%)

16 HOW SUPPLIED/STORAGE AND HANDLING

XEGLYZE is a white to off-white oil in water emulsion containing 0.74% [weight by weight] abametapir and supplied in a polyvinyl chloride (PVC) safety-coated single-use round amber glass bottle affixed with a polypropylene child resistant cap (NDC # 43598-921-11) featuring a tri-foil inner liner. The container is filled to a nominal 200 g (approximately 7 oz. or 210 mL) of the lotion.

Store upright at 20°C to 25°C (68°F to 77°F); excursions permitted to 15°C to 30°C (59°F and 86°F) [See USP Controlled Room Temperature].

Do not refrigerate or freeze.

17 PATIENT COUNSELING INFORMATION

Advise the patient or caregiver to read the FDA-approved patient labeling (Patient Information and Instructions for Use).

Inform the patient and caregiver of the following instructions:

- Do not ingest XEGLYZE.
- Keep out of reach of children. Use on children should be under the direct supervision of an adult because of the risk of benzyl alcohol toxicity [see Warnings and Precautions (5) and Use in Specific Populations (8.4)].
- Avoid contact with eyes.
- Wash hands after application.
- Hair may be shampooed any time after the treatment.
- Treatment with XEGLYZE involves a single application. Do not re-treat.
- Discard any unused portion. Do not flush contents down sink or toilet.

Manufactured by Groupe Parima Inc., for Dr. Reddy’s Laboratories, S.A. Elisabethenanlage 11, 4051 Basel, Switzerland

Distributed by Dr. Reddy’s Laboratories Inc., 107 College Road East, Princeton, NJ 08540

XeglyzeTM is a registered trademark of Dr. Reddy’s Laboratories, S.A.

Issued: 01 / 2022

Manufactured by Groupe Parima Inc., for Dr. Reddy’s Laboratories, S.A. Elisabethenanlage 11, 4051 Basel, Switzerland

Distributed by Dr. Reddy’s Laboratories Inc., 107 College Road East, Princeton, NJ 08540

XEGLYZETM is a registered trademark of Dr. Reddy’s Laboratories, S.A.

Issued: 01/2022

PATIENT INFORMATION
XEGLYZE (zeg’ lyze)
(abametapir)
Lotion

Important: XEGLYZE is for use on scalp hair and scalp only. Do not use XEGLYZE in your mouth, eyes, or vagina.

What is XEGLYZE?
XEGLYZE is a prescription medicine used to get rid of head lice in people 6 months of age and older. After XEGLYZE is rinsed off, a fine-tooth comb may be used to remove dead lice and nits from the hair and scalp. All personal items exposed to the hair or lice should be washed in hot water or dry-cleaned. See “How do I stop the spread of lice?” at the end of the XEGLYZE Instructions for Use.

It is not known if XEGLYZE is safe and effective in children under 6 months of age.

Before you use XEGLYZE, tell your healthcare provider if you or your child:

- have any skin conditions or sensitivities
- have any other medical conditions
- are pregnant or plan to become pregnant. It is not known if XEGLYZE can harm your unborn baby
- are breastfeeding or plan to breastfeed. It is not known if XEGLYZE passes into your breast milk.

How should I use XEGLYZE?
See the “Instructions for Use” for detailed information about the right way to apply XEGLYZE.

- Use XEGLYZE exactly as your healthcare provider tells you to use it. Your healthcare provider will prescribe the treatment that is right for you. Do not change your treatment without talking to your healthcare provider.
- Use XEGLYZE on dry hair.
- Completely cover all of your hair and scalp with XEGLYZE.
- Children will need an adult to apply XEGLYZE for them.
- Do not swallow XEGLYZE. If swallowed, call your Poison Control Center at 1-800-222-1222.
- Do not get XEGLYZE into your eyes. If XEGLYZE gets in your eye, gently flush with water. Wash your hands after you apply XEGLYZE.
- You may shampoo your hair any time after the treatment.
- When you complete your dose of XEGLYZE, do not use XEGLYZE again. Throw away any unused XEGLYZE. Do not flush XEGLYZE down sink or toilet.

What are the possible side effects of XEGLYZE?
The most common side effects of XEGLYZE include:

- Redness of the skin or scalp
- Rash
- Burning sensation of the skin
- Skin irritation

- Vomiting
- Eye irritation
- Itchy scalp
- Changes in your hair color

Tell your healthcare provider if you have any side effect that bothers you or that does not go away.
These are not all the possible side effects of XEGLYZE. For more information, ask your healthcare provider or pharmacist.
Call your doctor for medical advice about side effects. You may report side effects to the FDA at 1-800-FDA-1088.

How should I store XEGLYZE?

- Store upright at 20°C to 25°C (68°F to 77°F); excursions permitted to 15°C to 30°C (59°F and 86°F) [See USP Controlled Room Temperature].
- Do not refrigerate or freeze XEGLYZE.
- Discard (throw away) any unused product.

Keep XEGLYZE and all medicines out of reach of children.

General information about the safe and effective use of XEGLYZE
Medicines are sometimes prescribed for purposes other than those listed in a Patient Information leaflet. Do not use XEGLYZE for a condition for which it was not prescribed. Do not give XEGLYZE to other people, even if they have the same symptoms you have. It may harm them. You can also ask your pharmacist or healthcare provider for information about XEGLYZE that is written for health professionals.

What are the ingredients in XEGLYZE?
Active ingredient: abametapir
Inactive ingredients: benzyl alcohol 2.0%, butylated hydroxytoluene, carbomer homopolymer type C, light mineral oil, polysorbate 20, trolamine and water.

Manufactured by Groupe Parima, Inc., for Dr. Reddy’s Laboratories, S.A. Elisabethenanlage 11,
4051 Basel, Switzerland
XEGLYZE is a registered trademark of Dr. Reddy’s Laboratories, S.A.

Distributed by Dr. Reddy’s Laboratories, Inc.,
107 College Road East, Princeton, NJ 08540.

This Patient Information has been approved by the U.S. Food and Drug Administration

Issued: 01/2022

Instructions for Use

XEGLYZE (zeg' lyze)

(abametapir)

Lotion

Important: XEGLYZE is for use on scalp hair and scalp only. Do not use XEGLYZE in your mouth, eyes, or vagina.
Before you use XEGLYZE, it is important that you read the Patient Information and Instructions for Use. Be sure that you read, understand, and follow these Instructions for Use so that you use XEGLYZE the right way. Ask your healthcare provider or pharmacist if you have questions about the right way to use XEGLYZE.

Step 1: Your hair and scalp must be dry before you apply XEGLYZE. Shake XEGLYZE bottle well right before use.

Step 2: Remove the cap and apply XEGLYZE directly to dry hair and scalp.

Step 3: Completely cover your scalp and hair closest to the scalp first, and then apply outwards towards the ends of your hair.

Step 4: Rub XEGLYZE throughout your hair and scalp.
Use enough XEGLYZE to completely cover your entire scalp and all of your hair so that all lice and eggs are exposed to the lotion. You may need to use the full bottle. Be sure that each hair is coated from the scalp to the tip.

Step 5: Leave XEGLYZE on your hair and scalp for 10 minutes after it has been applied. Use a timer or clock. Start timing after you have completely covered your hair and scalp with XEGLYZE.
You or anyone who helps you apply XEGLYZE should wash their hands after application.

Step 6: After 10 minutes, rinse XEGLYZE from your hair and scalp with warm water.
A fine-tooth comb or special nit comb may be used to remove dead lice and nits.
You may shampoo your hair any time after the treatment.

How do I stop the spread of lice?

To help prevent the spread of lice from one person to another, here are some steps you can take:

- Avoid direct head-to-head contact with anyone known to have live, crawling lice.
- Do not share combs, brushes, hats, scarves, bandannas, ribbons, barrettes, hair bands, towels, helmets, or other hair-related personal items with anyone else, whether they have lice or not.
- Disinfect combs and brushes used by an infected person by soaking them in hot water (at least 130°F) for 5 to 10 minutes.
- Avoid sleepovers and slumber parties during lice outbreaks. Lice can live in bedding, pillows, and carpets that have recently been used by someone with lice.
- Machine wash and dry clothing, bed linens, and other items used by anyone having lice. Machine wash at high temperatures (130°F) and the high heat drying cycle. Clothing and items that are not washable can be dry-cleaned OR sealed in a plastic bag and stored for 2 weeks.

These Instructions for Use have been approved by the U.S. Food and Drug Administration.

Issued: 01/2022

CONTAINER LABEL

NDC 43598-921-11

Xeglyze (abametapir) Lotion, 0.74%

For topical use on the scalp hair and scalp only.

Rx only

200 g

CARTON LABEL

NDC 43598-921-11

Xeglyze (abametapir) Lotion, 0.74%

For topical use on the scalp hair and scalp only.

Rx only

200 g